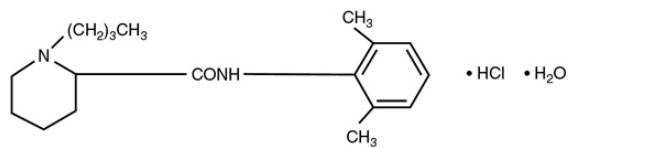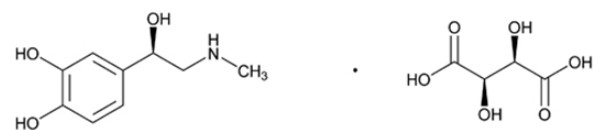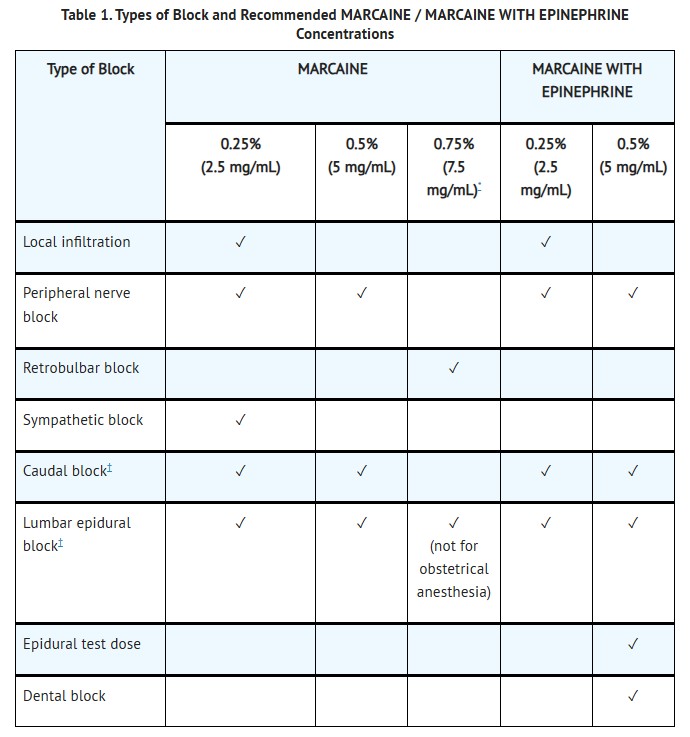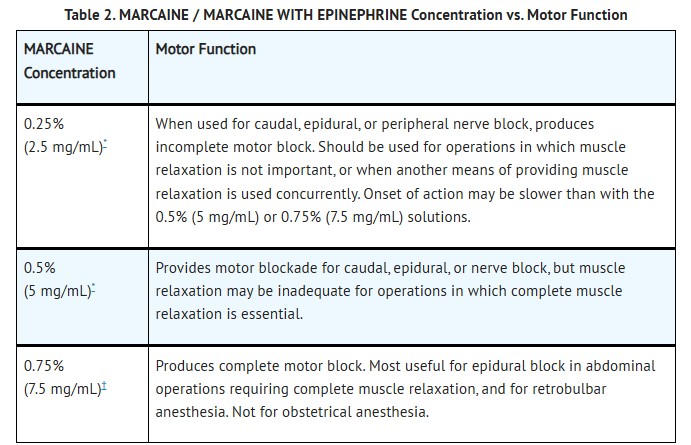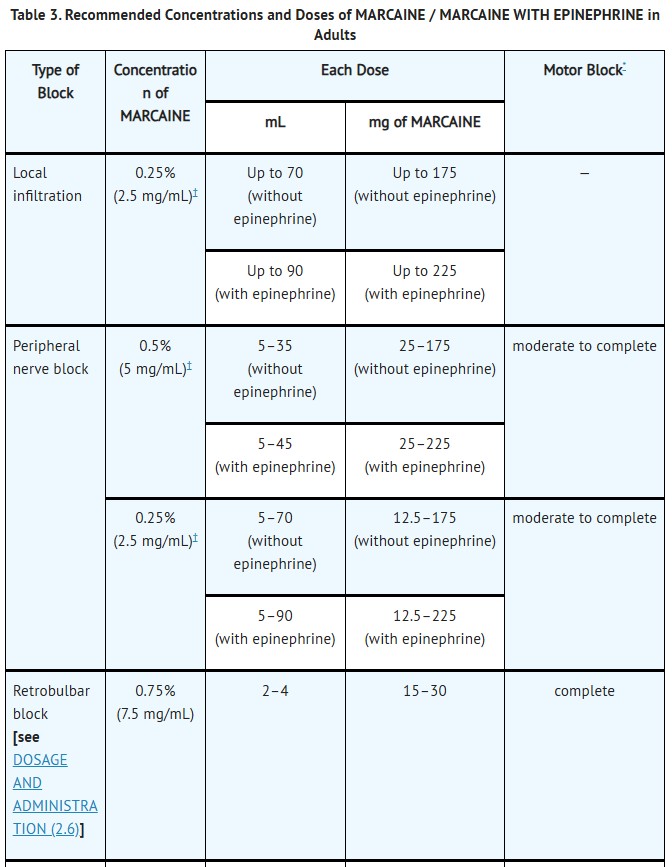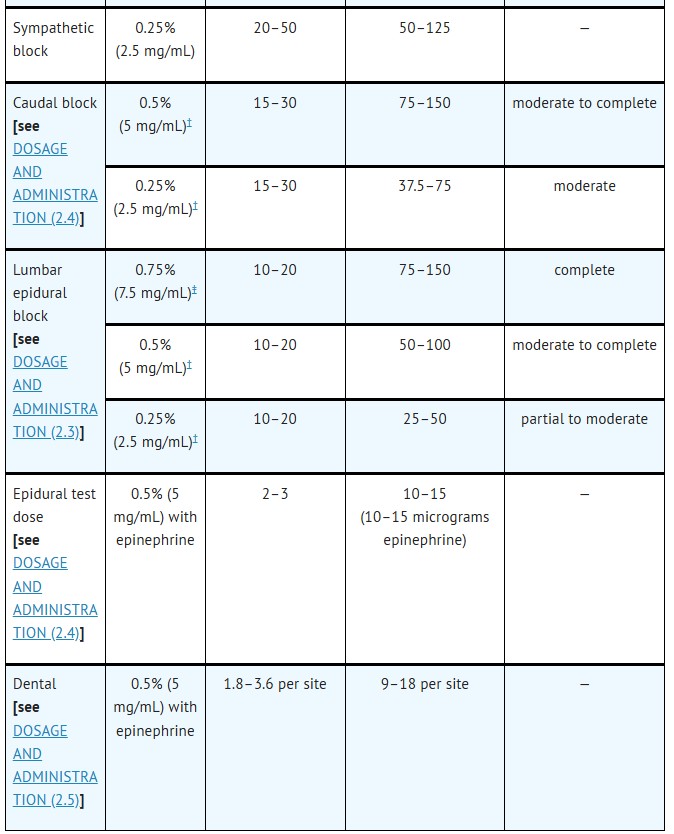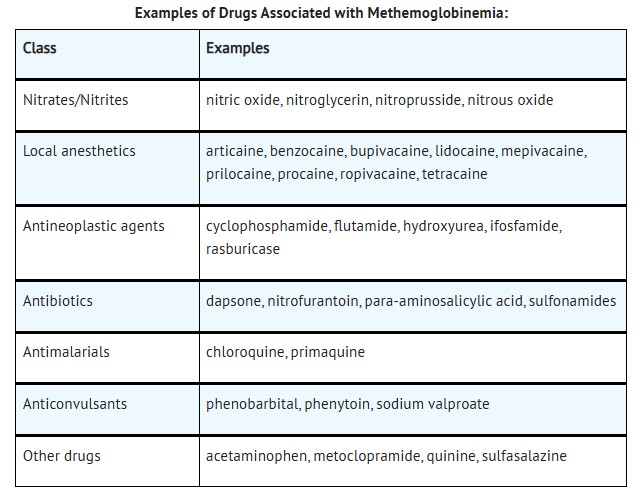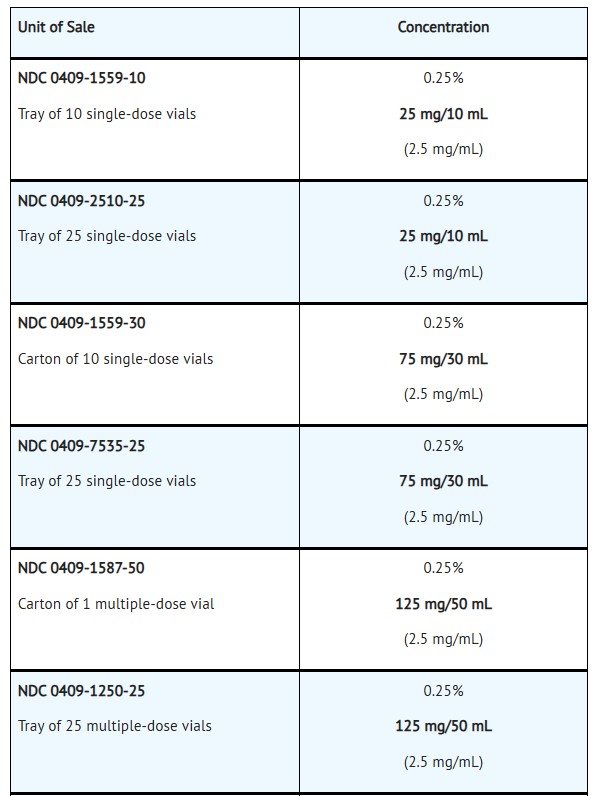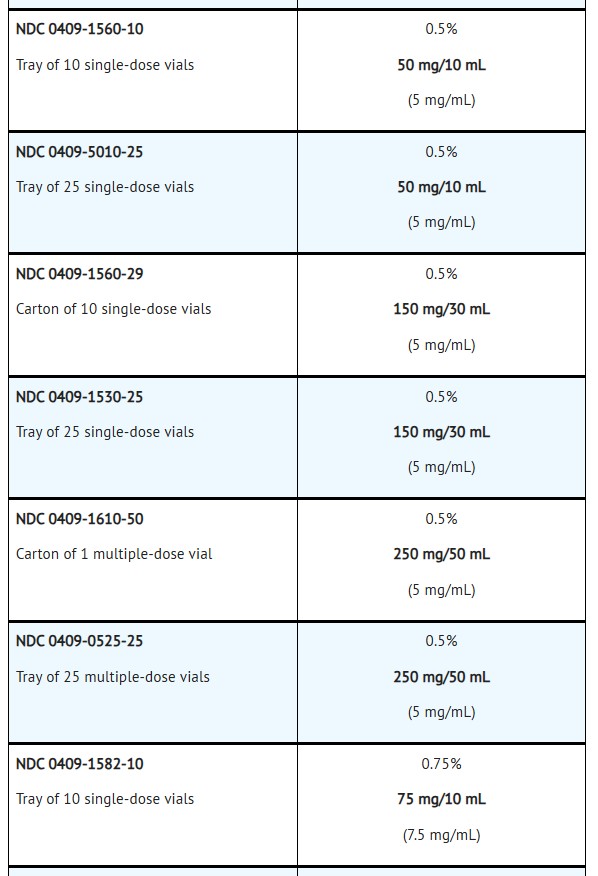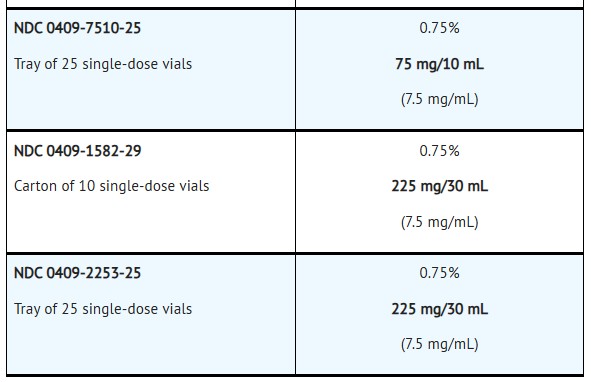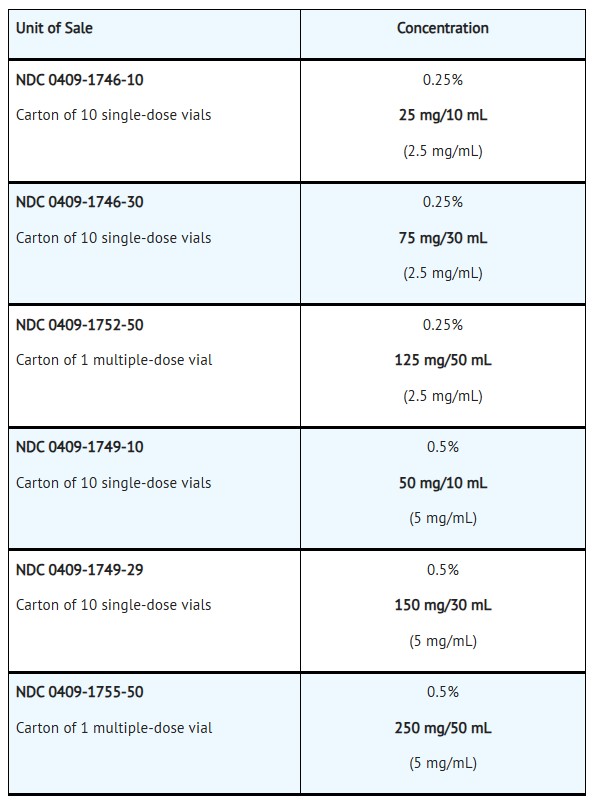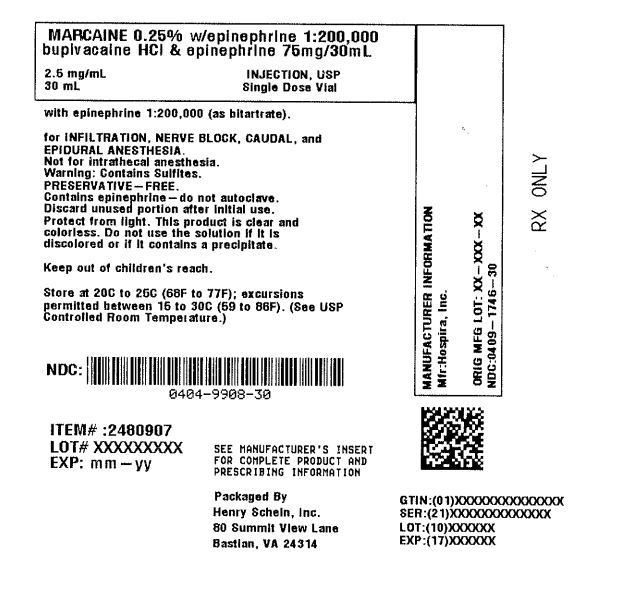 DRUG LABEL: MARCAINE WITH EPINEPHRINE
NDC: 0404-9908 | Form: INJECTION, SOLUTION
Manufacturer: Henry Schein, Inc.
Category: prescription | Type: HUMAN PRESCRIPTION DRUG LABEL
Date: 20260128

ACTIVE INGREDIENTS: BUPIVACAINE HYDROCHLORIDE 2.5 mg/1 mL; EPINEPHRINE BITARTRATE .0091 mg/1 mL
INACTIVE INGREDIENTS: SODIUM CHLORIDE; SODIUM HYDROXIDE; HYDROCHLORIC ACID; SODIUM METABISULFITE; SODIUM LACTATE; ASCORBIC ACID; EDETATE CALCIUM DISODIUM; WATER; MONOTHIOGLYCEROL

HIGHLIGHTS OF PRESCRIBING INFORMATION

These highlights do not include all the information needed to use MARCAINE™ and MARCAINE™ WITH EPINEPHRINE safely and effectively. See full prescribing information for MARCAINE™ and MARCAINE™ WITH EPINEPHRINE. MARCAINE™
MARCAINE™ (bupivacaine hydrochloride) injection, for infiltration, perineural, caudal, epidural, or retrobulbar use
MARCAINE™ WITH EPINEPHRINE (bupivacaine hydrochloride and epinephrine) injection, for infiltration, perineural, caudal, or epidural use
Initial U.S. Approval: 1972

Boxed Warning

WARNING: RISK OF CARDIAC ARREST WITH USE OF MARCAINE IN OBSTETRICAL ANESTHESIA

See full prescribing information for complete boxed warning.

There have been reports of cardiac arrest with difficult resuscitation or death during use of MARCAINE for epidural anesthesia in obstetrical patients. In most cases, this has followed use of the 0.75% (7.5 mg/mL) concentration. Resuscitation has been difficult or impossible despite apparently adequate preparation and appropriate management. Cardiac arrest has occurred after convulsions resulting from systemic toxicity, presumably following unintentional intravascular injection. The 0.75% (7.5 mg/mL) concentration of MARCAINE is not recommended for obstetrical anesthesia and should be reserved for surgical procedures where a high degree of muscle relaxation and prolonged effect are necessary (5.1).

1 Indications And Usage

MARCAINE contains bupivacaine, an amide local anesthetic, and MARCAINE WITH EPINEPHRINE is a combination of bupivacaine, an amide local anesthetic, and epinephrine, an alpha and beta-adrenergic agonist. MARCAINE / MARCAINE WITH EPINEPHRINE is indicated in adults for the production of local or regional anesthesia or analgesia for surgery, dental and oral surgery procedures, diagnostic and therapeutic procedures, and for obstetrical procedures. For each type of block indicated to produce local or regional anesthesia or analgesia, specific concentrations and presentations are recommended. (1, 2.2)

Limitations of Use

Not all blocks are indicated for use with MARCAINE / MARCAINE WITH EPINEPHRINE given clinically significant risks associated with use. (1, 2.2, 4, 5.1, 5.4, 5.5, 5.7, 5.9)

2 Dosage and Administration

- Not for intrathecal use. (2.1)
- Avoid use of solutions containing antimicrobial preservatives (i.e., multiple-dose vials) for epidural or caudal anesthesia. (2.1, 5.4)
- Three mL of MARCAINE WITH EPINEPHRINE without antimicrobial preservative (0.5% bupivacaine with 1:200,000 epinephrine) is recommended for use as a test dose prior to caudal and lumbar epidural blocks when clinical conditions permit. (2.4)
- See full prescribing information for:
- Recommended concentrations and dosages of MARCAINE / MARCAINE WITH EPINEPHRINE according to type of block. (2.2)
- Additional dosage and administration information pertaining to use in epidural anesthesia, test dose for caudal and lumbar epidural blocks, use in dentistry, and use in ophthalmic surgery. (2.3, 2.4, 2.5, 2.6)

3 Dosage Forms And Strengths

MARCAINE injection and MARCAINE WITH EPINEPHRINE injection are available in multiple concentrations. See full prescribing information for detailed description of each formulation. (3)

4 Contraindications

- Obstetrical paracervical block anesthesia. Its use in this technique has resulted in fetal bradycardia and death. (4)
- Intravenous regional anesthesia (Bier Block). (4)
- Known hypersensitivity to bupivacaine or to any local anesthetic agent of the amide-type or to other components of MARCAINE / MARCAINE WITH EPINEPHRINE. (4)

5 Warnings And Precautions

- Dose-Related Toxicity: Monitor cardiovascular and respiratory vital signs and patient's state of consciousness after injection of MARCAINE / MARCAINE WITH EPINEPHRINE. (5.2)
- Methemoglobinemia: Cases of methemoglobinemia have been reported in association with local anesthetic use. See full prescribing information for more detail on managing these risks. (5.3)
- Chondrolysis with Intra-Articular Infusion: Intra-articular infusions of local anesthetics including MARCAINE following arthroscopic and other surgical procedures is an unapproved use, and there have been post-marketing reports of chondrolysis in patients receiving such infusions. (5.5)
- Risk of Cardiac Arrest with Intravenous Regional Anesthesia Use (Bier Block): There have been reports of cardiac arrest and death during the use of bupivacaine for intravenous regional anesthesia (Bier Block). (5.7)
- Allergic-Type Reactions to Sulfites in MARCAINE WITH EPINEPHRINE: MARCAINE WITH EPINEPHRINE contains sodium metabisulfite, a sulfite that may cause allergic-type reactions including anaphylactic symptoms and life-threatening or less severe asthmatic episodes in certain susceptible people. (5.8)
- Risk of Systemic Toxicities with Unintended Intravascular or Intrathecal Injection: Unintended intravascular or intrathecal injection may be associated with systemic toxicities, including CNS or cardiorespiratory depression and coma, progressing ultimately to respiratory arrest. Aspirate for blood or cerebrospinal fluid (where applicable) prior to each dose and consider using a test dose of MARCAINE WITH EPINEPHRINE. (5.9)

6 Adverse Reactions

Most common adverse reactions are related to the central nervous system and the cardiovascular system. (6)

To report SUSPECTED ADVERSE REACTIONS, contact Pfizer Inc. at 1-800-438-1985 or FDA at 1-800-FDA-1088 or www.fda.gov/medwatch.

7 Drug Interactions

- Local Anesthetics: The toxic effects of local anesthetics are additive. Monitor for neurologic and cardiovascular effects when additional local anesthetics are administered. (7.1)
- Monoamine Oxidase Inhibitors and Tricyclic Antidepressants: Administration of MARCAINE WITH EPINEPHRINE to patients receiving monoamine oxidase inhibitors or tricyclic antidepressants may produce severe, prolonged hypertension. Concurrent use of these agents should generally be avoided. (5.6, 7.2)
- Ergot-Type Oxytocic Drugs: Concurrent administration of MARCAINE WITH EPINEPHRINE and ergot-type oxytocic drugs may cause severe, persistent hypertension or cerebrovascular accidents. (5.6, 7.3)
- Nonselective Beta-Adrenergic Antagonists: Administration of MARCAINE WITH EPINEPHRINE (containing a vasoconstrictor) in patients receiving nonselective beta-adrenergic antagonists may cause severe hypertension and bradycardia. Concurrent use of these agents should generally be avoided. (5.6, 7.4)
- Drugs Associated with Methemoglobinemia: Patients are at increased risk of developing methemoglobinemia when concurrently exposed to nitrates, nitrites, local anesthetics, antineoplastic agents, antibiotics, antimalarials, anticonvulsants, and other drugs. (7.5)
- Potent Inhalation Anesthetics: Serious dose-related cardiac arrhythmias may occur if preparations containing a vasoconstrictor such as epinephrine are used in patients during or following the administration of potent inhalation anesthetics. (5.13, 7.6)

8 USE IN SPECIFIC POPULATIONS

- Pediatric Use: Administration of MARCAINE / MARCAINE WITH EPINEPHRINE in pediatric patients younger than 12 years is not recommended. (8.4)
- Geriatric Use: Patients 65 years and over, particularly those with hypertension, may be at increased risk for developing hypotension while undergoing anesthesia with MARCAINE / MARCAINE WITH EPINEPHRINE. (8.5)
- Moderate to Severe Hepatic Impairment: Consider increased monitoring for bupivacaine systemic toxicity. (8.6)

See 17 for PATIENT COUNSELING INFORMATION.

Revised: 7/2023

FULL PRESCRIBING INFORMATION

Boxed Warning

WARNING: RISK OF CARDIAC ARREST WITH USE OF MARCAINE IN OBSTETRICAL ANESTHESIA

See full prescribing information for complete boxed warning.

There have been reports of cardiac arrest with difficult resuscitation or death during use of MARCAINE for epidural anesthesia in obstetrical patients. In most cases, this has followed use of the 0.75% (7.5 mg/mL) concentration. Resuscitation has been difficult or impossible despite apparently adequate preparation and appropriate management. Cardiac arrest has occurred after convulsions resulting from systemic toxicity, presumably following unintentional intravascular injection. The 0.75% (7.5 mg/mL) concentration of MARCAINE is not recommended for obstetrical anesthesia and should be reserved for surgical procedures where a high degree of muscle relaxation and prolonged effect are necessary (5.1).

1 Indications And Usage

MARCAINE / MARCAINE WITH EPINEPHRINE is indicated in adults for the production of local or regional anesthesia or analgesia for surgery, dental and oral surgery procedures, diagnostic and therapeutic procedures, and for obstetrical procedures. Specific concentrations and presentations of MARCAINE / MARCAINE WITH EPINEPHRINE are recommended for each type of block indicated to produce local or regional anesthesia or analgesia [see Dosage and Administration (2.2)].

Limitations of Use

Not all blocks are indicated for use with MARCAINE / MARCAINE WITH EPINEPHRINE given clinically significant risks associated with use [see Dosage and Administration (2.2), Contraindications (4), Warnings and Precautions (5.1, 5.4, 5.5, 5.7, 5.9)].

2 Dosage and Administration

2.1 Important Dosage and Administration Information

•MARCAINE / MARCAINE WITH EPINEPHRINE is not for intrathecal use.
•Avoid use of MARCAINE / MARCAINE WITH EPINEPHRINE solutions containing antimicrobial preservatives (i.e., multiple-dose vials) for epidural or caudal anesthesia [see Warnings and Precautions (5.4)].
•Discard unused portions of solution not containing preservatives, i.e., those supplied in single-dose vials, following initial use.
•Visually inspect this product for particulate matter and discoloration prior to administration whenever solution and container permit. MARCAINE / MARCAINE WITH EPINEPHRINE are clear, colorless solutions. Do not administer solutions which are discolored or contain particulate matter.
•Mixing or the prior or intercurrent use of any other local anesthetic with MARCAINE / MARCAINE WITH EPINEPHRINE is not recommended because of insufficient data on the clinical use of such mixtures.

Administration Precautions

•MARCAINE / MARCAINE WITH EPINEPHRINE are to be administered in carefully adjusted dosages by or under the supervision of experienced clinicians who are well versed in the diagnosis and management of dose-related toxicity and other acute emergencies which might arise from the block to be employed.
•Use MARCAINE / MARCAINE WITH EPINEPHRINE only if the following are immediately available: oxygen, cardiopulmonary resuscitative equipment and drugs, and the personnel resources needed for proper management of toxic reactions and related emergencies [see Warnings and Precautions (5.2), Adverse Reactions (6), Overdosage (10)].
•The toxic effects of local anesthetics are additive. Monitor for neurologic and cardiovascular effects related to local anesthetic systemic toxicity when additional local anesthetics are administered with MARCAINE / MARCAINE WITH EPINEPHRINE [see Warnings and Precautions (5.2), Drug Interactions (7.1), Overdosage (10)].
•Aspirate for blood or cerebrospinal fluid (where applicable) prior to injecting MARCAINE / MARCAINE WITH EPINEPHRINE, both the initial dose and all subsequent doses, to avoid intravascular or intrathecal injection. However, a negative aspiration for blood or cerebrospinal fluid does not ensure against an intravascular or intrathecal injection [see Warnings and Precautions (5.9)].
•Avoid rapid injection of a large volume of MARCAINE / MARCAINE WITH EPINEPHRINE and use fractional (incremental) doses when feasible.
•During major regional nerve blocks, such as those of the brachial plexus or lower extremity, the patient should have an indwelling intravenous catheter to assure adequate intravenous access. The lowest dosage of MARCAINE / MARCAINE WITH EPINEPHRINE that results in effective anesthesia should be used to avoid high plasma levels and serious adverse reactions.
•Perform careful and constant monitoring of cardiovascular and respiratory (adequacy of oxygenation and ventilation) vital signs and the patient's level of consciousness after each local anesthetic injection.
•Use MARCAINE WITH EPINEPHRINE in carefully restricted quantities in areas of the body supplied by end arteries or having otherwise compromised blood supply such as digits, nose, external ear, or penis [see Warnings and Precautions (5.12)].

2.2 Recommended Concentrations and Dosages of MARCAINE / MARCAINE WITH EPINEPHRINE

The dosage of MARCAINE / MARCAINE WITH EPINEPHRINE administered varies with the anesthetic procedure, the area to be anesthetized, the vascularity of the tissues, the number of neuronal segments to be blocked, the depth of anesthesia and degree of muscle relaxation required, the duration of anesthesia desired, individual tolerance, and the physical condition of the patient. Administer the smallest dosage and concentration required to produce the desired result.

✓= indicated use [see Warnings and Precautions (5.1)].
*MARCAINE 0.75% (7.5 mg/mL) is not recommended for nonobstetrical surgical procedures in pregnant patients.

**Avoid use of multiple-dose vials of MARCAINE and MARCAINE WITH EPINEPHRINE for caudal or epidural anesthesia [see Warnings and Precautions (5.4)].

At recommended dosages, MARCAINE / MARCAINE WITH EPINEPHRINE produces complete sensory block, but the effect on motor function differs among the three concentrations. Table 2 provides information on the expected effect on motor function for the three concentrations.

*These products include MARCAINE and MARCAINE WITH EPINEPHRINE [the epinephrine concentration (1:200,000) is not included in the table].

**These are only MARCAINE products [there is no 0.75% (7.5 mg/mL) concentration for MARCAINE WITH EPINEPHRINE].

The duration of anesthesia with MARCAINE / MARCAINE WITH EPINEPHRINE is such that for most indications, a single dose is sufficient.

The maximum dosage limit within the recommended dosage range must be individualized in each case after evaluating the size and physical status of the patient, as well as the anticipated rate of systemic absorption from a particular injection site.

The dosages in Table 3 are recommended as a guide for use in the average adult. These doses may be repeated once every three hours. Do not exceed a total daily dosage of 400 mg in 24 hours. The duration of anesthetic effect may be prolonged by the addition of epinephrine.

a. With continuous (intermittent) techniques, repeat doses increase the degree of motor block. The first repeat dose of 0.5% (5 mg/mL) may produce complete motor block. Intercostal nerve block with 0.25% (2.5 mg/mL) also may produce complete motor block for intra-thoracic and upper intra-abdominal surgery.

b.Solutions with or without epinephrine (i.e., applies to MARCAINE and MARCAINE WITH EPINEPHRINE). The MARCAINE WITH EPINEPHRINE products include epinephrine (1:200,000).

c.For single-dose use; not for intermittent epidural technique. Not for obstetrical anesthesia.

2.3 Use in Epidural Anesthesia

During the administration of epidural anesthesia, it is recommended that a test dose of MARCAINE WITH EPINEPHRINE without antimicrobial preservative (0.5% bupivacaine with 1:200,000 epinephrine) be administered initially and the effects monitored before the full dose is given. When using a "continuous" catheter technique, test doses should be given prior to both the initial and all supplemental doses, because a catheter in the epidural space can migrate into a blood vessel or through the dura [see Dosage and Administration (2.4)].

During epidural administration, administer MARCAINE / MARCAINE WITH EPINEPHRINE, 0.5% (5 mg/mL) and MARCAINE 0.75% (7.5 mg/mL) solutions in incremental doses of 3 mL to 5 mL with sufficient time between doses to detect toxic manifestations of unintentional intravascular or intrathecal injection. Administer injections slowly, with frequent aspirations before and during the injection to avoid intravascular injection. Perform syringe aspirations before and during each supplemental injection in continuous (intermittent) catheter techniques. In obstetrics, use ONLY the 0.5% (5 mg/mL) and 0.25% (2.5 mg/mL) concentrations of MARCAINE / MARCAINE WITH EPINEPHRINE [see Warnings and Precautions (5.1)]; incremental doses of 3 mL to 5 mL of the 0.5% (5 mg/mL) solution not exceeding 50 mg to 100 mg at any dosing interval are recommended. Repeat doses should be preceded by a test dose containing epinephrine if not clinically contraindicated. Use only the single-dose vials for caudal or epidural anesthesia; avoid use of the multiple-dose vials for these procedures, which contain a preservative [see Dosage and Administration (2.1, 2.4), Warnings and Precautions (5.4, 5.9)].

2.4 Test Dose for Caudal and Lumbar Epidural Blocks

Three mL of MARCAINE WITH EPINEPHRINE without antimicrobial preservative (0.5% bupivacaine with 1:200,000 epinephrine) is recommended for use as a test dose prior to caudal and lumbar epidural blocks when clinical conditions permit. This test dose may serve as a warning of unintended intravascular or intrathecal injection. Closely monitor for early clinical signs of toxicity following each test dose [see Warnings and Precautions (5.9)]. Allot adequate time for onset of spinal block to detect possible intrathecal injection. An intravascular or intrathecal injection is still possible even if results of the test dose are negative. The test dose itself may produce a systemic toxic reaction, high spinal, or cardiovascular effects from the epinephrine [see Warnings and Precautions (5.2, 5.9), Overdosage (10)].

2.5 Use in Dentistry

MARCAINE WITH EPINEPHRINE 0.5% (5 mg/mL) is recommended for infiltration and block injection in the maxillary and mandibular area when a longer duration of local anesthesia is desired, such as for procedures generally associated with significant postoperative pain. The average dose of 1.8 mL (9 mg) per injection site will usually suffice; an occasional second dose of 1.8 mL (9 mg) may be used if necessary to produce adequate anesthesia after allowing 2 to 10 minutes for block onset [see Clinical Pharmacology (12.2)]. Use the lowest effective dose and allow time between injections; it is recommended that the total dose for all injection sites, spread out over a single dental sitting, not exceed 90 mg for a healthy adult patient (ten 1.8 mL injections of 0.5% (5 mg/mL) MARCAINE WITH EPINEPHRINE). Inject slowly and with frequent aspirations.

2.6 Use in Ophthalmic Surgery

When MARCAINE 0.75% (7.5 mg/mL) is used for retrobulbar block, complete corneal anesthesia usually precedes onset of clinically acceptable external ocular muscle akinesia. Therefore, presence of akinesia rather than anesthesia alone should determine readiness of the patient for surgery [see Warnings and Precautions (5.15)].

3 Dosage Forms And Strengths

MARCAINE (bupivacaine hydrochloride) injection is a clear, colorless solution available as:

- 0.25% (25 mg/10 mL) (2.5 mg/mL) in single-dose vials.
- 0.25% (75 mg/30 mL) (2.5 mg/mL) in single-dose vials.
- 0.25% (125 mg/50 mL) (2.5 mg/mL) in multiple-dose vials.
- 0.5% (50 mg/10 mL) (5 mg/mL) in single-dose vials.
- 0.5% (150 mg/30 mL) (5 mg/mL) in single-dose vials.
- 0.5% (250 mg/50 mL) (5 mg/mL) in multiple-dose vials.
- 0.75% (75 mg/10 mL) (7.5 mg/mL) in single-dose vials.
- 0.75% (225 mg/30 mL) (7.5 mg/mL) in single-dose vials.

MARCAINE with 1:200,000 epinephrine (bupivacaine hydrochloride and epinephrine) injection is a clear, colorless solution available as:

- 0.25% (25 mg/10 mL) (2.5 mg/mL) in single-dose vials.
- 0.25% (75 mg/30 mL) (2.5 mg/mL) in single-dose vials.
- 0.25% (125 mg/50 mL) (2.5 mg/mL) in multiple-dose vials.
- 0.5% (50 mg/10mL) (5 mg/mL) in single-dose vials.
- 0.5% (150 mg/30 mL) (5 mg/mL) in single-dose vials.
- 0.5% (250 mg/50 mL) (5 mg/mL) in multiple-dose vials.

4 Contraindications

MARCAINE / MARCAINE WITH EPINEPHRINE is contraindicated in:

- obstetrical paracervical block anesthesia. Its use in this technique has resulted in fetal bradycardia and death.
- intravenous regional anesthesia (Bier Block) [see Warnings and Precautions (5.7)].
- patients with a known hypersensitivity to bupivacaine or to any local anesthetic agent of the amide-type or to other components of MARCAINE / MARCAINE WITH EPINEPHRINE.

5 Warnings And Precautions

5.1 Risk of Cardiac Arrest with Use of MARCAINE in Obstetrical Anesthesia

There have been reports of cardiac arrest with difficult resuscitation or death during use of MARCAINE for epidural anesthesia in obstetrical patients. In most cases, this has followed use of the 0.75% (7.5 mg/mL) concentration. Resuscitation has been difficult or impossible despite apparently adequate preparation and appropriate management. Cardiac arrest has occurred after convulsions resulting from systemic toxicity, presumably following unintentional intravascular injection. The 0.75% (7.5 mg/mL) concentration of MARCAINE is not recommended for obstetrical anesthesia and should be reserved for surgical procedures where a high degree of muscle relaxation and prolonged effect are necessary.

5.2 Dose-Related Toxicity

The safety and effectiveness of MARCAINE / MARCAINE WITH EPINEPHRINE depend on proper dosage, correct technique, adequate precautions, and readiness for emergencies. Careful and constant monitoring of cardiovascular and respiratory (adequacy of ventilation) vital signs and the patient's state of consciousness should be performed after injection of MARCAINE / MARCAINE WITH EPINEPHRINE solutions.

Possible early warning signs of central nervous system (CNS) toxicity are restlessness, anxiety, incoherent speech, lightheadedness, numbness and tingling of the mouth and lips, metallic taste, tinnitus, dizziness, blurred vision, tremors, twitching, CNS depression, or drowsiness. Delay in proper management of dose-related toxicity, underventilation from any cause, and/or altered sensitivity may lead to the development of acidosis, cardiac arrest, and, possibly, death.

During major regional nerve blocks, such as those of the brachial plexus or lower extremity, the patient should have an indwelling intravenous catheter to assure adequate intravenous access. Use the lowest dosage of MARCAINE / MARCAINE WITH EPINEPHRINE that results in effective anesthesia to avoid high plasma levels and serious adverse effects. Avoid rapid injection of a large volume of MARCAINE / MARCAINE WITH EPINEPHRINE solution and administer fractional (incremental) doses when feasible.

Injection of repeated doses of MARCAINE / MARCAINE WITH EPINEPHRINE may cause significant increases in plasma levels with each repeated dose due to slow accumulation of the drug or its metabolites, or to slow metabolic degradation. Tolerance to elevated blood levels varies with the status of the patient. Debilitated, elderly patients and acutely ill patients should be given reduced doses commensurate with their age and physical status.

5.3 Methemoglobinemia

Cases of methemoglobinemia have been reported in association with local anesthetic use. Although all patients are at risk for methemoglobinemia, patients with glucose-6-phosphate dehydrogenase deficiency, congenital or idiopathic methemoglobinemia, cardiac or pulmonary compromise, infants under 6 months of age, and concurrent exposure to oxidizing agents or their metabolites are more susceptible to developing clinical manifestations of the condition [see Drug Interactions (7.5)]. If local anesthetics must be used in these patients, close monitoring for symptoms and signs of methemoglobinemia is recommended.

Signs of methemoglobinemia may occur immediately or may be delayed some hours after exposure, and are characterized by a cyanotic skin discoloration and/or abnormal coloration of the blood. Methemoglobin levels may continue to rise; therefore, immediate treatment is required to avert more serious CNS and cardiovascular adverse effects, including seizures, coma, arrhythmias, and death. Discontinue MARCAINE / MARCAINE WITH EPINEPHRINE and any other oxidizing agents. Depending on the severity of the signs and symptoms, patients may respond to supportive care, i.e., oxygen therapy, hydration. A more severe clinical presentation may require treatment with methylene blue, exchange transfusion, or hyperbaric oxygen.

5.4 Antimicrobial Preservatives in Multiple-Dose Vials

Avoid use of MARCAINE / MARCAINE WITH EPINEPHRINE solutions containing antimicrobial preservatives, i.e., those supplied in multiple-dose vials, for epidural or caudal anesthesia because safety has not been established with such use.

5.5 Chondrolysis with Intra-Articular Infusion

Intra-articular infusions of local anesthetics including MARCAINE following arthroscopic and other surgical procedures is an unapproved use, and there have been post-marketing reports of chondrolysis in patients receiving such infusions. The majority of reported cases of chondrolysis have involved the shoulder joint; cases of gleno-humeral chondrolysis have been described in pediatric and adult patients following intra-articular infusions of local anesthetics with and without epinephrine for periods of 48 to 72 hours. There is insufficient information to determine whether shorter infusion periods are associated with chondrolysis. The time of onset of symptoms, such as joint pain, stiffness and loss of motion can be variable, but may begin as early as the 2nd month after surgery. Currently, there is no effective treatment for chondrolysis; patients who experienced chondrolysis have required additional diagnostic and therapeutic procedures and some required arthroplasty or shoulder replacement.

5.6 Risk of Adverse Reactions Due to Drug Interactions with MARCAINE WITH EPINEPHRINE

Risk of Severe, Persistent Hypertension Due to Drug Interactions Between MARCAINE WITH EPINEPHRINE and Monoamine Oxidase Inhibitors and Tricyclic Antidepressants

Administration of MARCAINE WITH EPINEPHRINE (containing a vasoconstrictor) in patients receiving monoamine oxidase inhibitors (MAOI) or tricyclic antidepressants may result in severe, prolonged hypertension. Concurrent use of these agents should generally be avoided. In situations when concurrent therapy is necessary, careful monitoring of the patient's hemodynamic status is essential [see Drug Interactions (7.2)].

Risk of Severe, Persistent Hypertension or Cerebrovascular Accidents Due to Drug Interactions Between MARCAINE WITH EPINEPHRINE and Ergot-Type Oxytocic Drugs

Concurrent administration of MARCAINE WITH EPINEPHRINE and ergot-type oxytocic drugs may cause severe, persistent hypertension or cerebrovascular accidents. Avoid use of MARCAINE WITH EPINEPHRINE concomitantly with ergot-type oxytocic drugs [see Drug Interactions (7.3)].

Risk of Hypertension and Bradycardia Due to Drug Interactions Between MARCAINE WITH EPINEPHRINE and Nonselective Beta-Adrenergic Antagonists

Administration of MARCAINE WITH EPINEPHRINE (containing a vasoconstrictor) in patients receiving nonselective beta-adrenergic antagonists may cause severe hypertension and bradycardia. Concurrent use of these agents should generally be avoided. In situations when concurrent therapy is necessary, careful monitoring of the patient's blood pressure and heart rate is essential [see Drug Interactions (7.4)].

5.7 Risk of Cardiac Arrest with Intravenous Regional Anesthesia Use (Bier Block)

There have been reports of cardiac arrest and death during the use of bupivacaine for intravenous regional anesthesia (Bier Block). Information on safe dosages and techniques of administration of MARCAINE in this procedure is lacking. Therefore, MARCAINE / MARCAINE WITH EPINEPHRINE is contraindicated for use with this technique [see Contraindications (4)].

5.8 Allergic-Type Reactions to Sulfites in MARCAINE WITH EPINEPHRINE

MARCAINE WITH EPINEPHRINE contains sodium metabisulfite, a sulfite that may cause allergic-type reactions including anaphylactic symptoms and life-threatening or less severe asthmatic episodes in certain susceptible people. The overall prevalence of sulfite sensitivity in the general population is unknown and probably low. Sulfite sensitivity is seen more frequently in asthmatic than in nonasthmatic people. MARCAINE without epinephrine does not contain sodium metabisulfite.

5.9 Risk of Systemic Toxicities with Unintended Intravascular or Intrathecal Injection

Unintended intravascular or intrathecal injection of MARCAINE / MARCAINE WITH EPINEPHRINE may be associated with systemic toxicities, including CNS or cardiorespiratory depression and coma, progressing ultimately to respiratory arrest. Unintentional intrathecal injection during the intended performance of caudal or lumbar epidural block or nerve blocks near the vertebral column has resulted in underventilation or apnea ("Total or High Spinal"). A high spinal has been characterized by paralysis of the legs, loss of consciousness, respiratory paralysis, and bradycardia [see Adverse Reactions (6)].

Aspirate for blood or cerebrospinal fluid (where applicable) before injecting MARCAINE / MARCAINE WITH EPINEPHRINE, both the initial dose and all subsequent doses, to avoid intravascular or intrathecal injection. However, a negative aspiration for blood or cerebrospinal fluid does not ensure against an intravascular or intrathecal injection.

Use of Test Dose with Epidural Anesthesia

To serve as a warning of unintended intravascular or intrathecal injection, 3 mL of MARCAINE WITH EPINEPHRINE without antimicrobial preservative (0.5% bupivacaine with 1:200,000 epinephrine) may be used as a test dose prior to administration of the full dose in caudal and lumbar epidural blocks [see Dosage and Administration (2.4)]. Three mL of MARCAINE WITH EPINEPHRINE without antimicrobial preservative (0.5% bupivacaine with 1:200,000 epinephrine) contains 15 mg bupivacaine and 15 mcg epinephrine. An intravascular or intrathecal injection is still possible even if results of the test dose are negative.

Signs/symptoms of unintended intravascular or intrathecal injection of the test dose of MARCAINE WITH EPINEPHRINE and monitoring recommendations are described below.

- Unintended intravascular injection: Likely to produce a transient "epinephrine response" within 45 seconds, consisting of an increase in heart rate and/or systolic blood pressure, circumoral pallor, palpitations, and nervousness in the unsedated patient. The sedated patient may exhibit only a pulse rate increase of 20 or more beats per minute for 15 or more seconds. Therefore, following the test dose, the heart rate should be monitored for increases. Patients on beta-blockers may not manifest changes in heart rate, but blood pressure monitoring can detect a transient rise in systolic blood pressure.
- Unintended intrathecal injection: Evidenced within a few minutes by signs of spinal block (e.g., decreased sensation of the buttocks, paresis of the legs, or, in the sedated patient, absent knee jerk).

The test dose itself may produce a systemic toxic reaction, high spinal or epinephrine-induced cardiovascular effects [see Overdosage (10)].

5.10 Risk of Toxicity in Patients with Hepatic Impairment

Because amide local anesthetics such as bupivacaine are metabolized by the liver, consider reduced dosing and increased monitoring for bupivacaine systemic toxicity in patients with moderate to severe hepatic impairment who are treated with MARCAINE / MARCAINE WITH EPINEPHRINE, especially with repeat doses [see Use in Specific Populations (8.6)].

5.11 Risk of Use in Patients with Impaired Cardiovascular Function

MARCAINE / MARCAINE WITH EPINEPHRINE should be given in reduced doses in patients with impaired cardiovascular function (e.g., hypotension, heartblock) because they may be less able to compensate for functional changes associated with the prolongation of AV conduction produced by MARCAINE / MARCAINE WITH EPINEPHRINE. Monitor patients closely for blood pressure, heart rate, and ECG changes.

5.12 Risk of Ischemic Injury or Necrosis in Body Areas with Limited Blood Supply

Use MARCAINE WITH EPINEPHRINE in carefully restricted quantities in areas of the body supplied by end arteries or having otherwise compromised blood supply such as digits, nose, external ear, or penis. Patients with hypertensive vascular disease may exhibit exaggerated vasoconstrictor response. Ischemic injury or necrosis may result.

5.13 Risk of Cardiac Arrhythmias with Concomitant Use of Potent Inhalation Anesthetics

Serious dose-related cardiac arrhythmias may occur if preparations containing a vasoconstrictor such as epinephrine (e.g., MARCAINE WITH EPINEPHRINE) are used in patients during or following the administration of potent inhalation anesthetics [see Drug Interactions (7.6)]. In deciding whether to concurrently use MARCAINE WITH EPINEPHRINE with potent inhalation anesthetics in the same patient, the combined action of both agents upon the myocardium, the concentration and volume of vasoconstrictor used, and the time since injection, when applicable, should be taken into account.

5.14 Risk of Adverse Reactions with Use in Head and Neck Area

Small doses of local anesthetics (e.g., MARCAINE) injected into the head and neck area, including retrobulbar, dental, and stellate ganglion blocks, may produce adverse reactions similar to systemic toxicity seen with unintentional intravascular injections of larger doses. The injection procedures require the utmost care. Confusion, convulsions, respiratory depression, and/or respiratory arrest, and cardiovascular stimulation or depression have been reported. These reactions may be due to intra-arterial injection of the local anesthetic with retrograde flow to the cerebral circulation. They may also be due to puncture of the dural sheath of the optic nerve during retrobulbar block with diffusion of any local anesthetic along the subdural space to the midbrain. Monitor circulation and respiration and constantly observe patients receiving MARCAINE / MARCAINE WITH EPINEPHRINE blocks. Resuscitative equipment and drugs, and personnel for treating adverse reactions should be immediately available. Dosage recommendations should not be exceeded [see Dosage and Administration (2.2)].

5.15 Risk of Respiratory Arrest with Use in Ophthalmic Surgery

Clinicians who perform retrobulbar blocks should be aware that there have been reports of respiratory arrest following local anesthetic injection. Prior to retrobulbar block (e.g., with MARCAINE / MARCAINE WITH EPINEPHRINE), as with all other regional procedures, resuscitative equipment and drugs, and personnel to manage respiratory arrest or depression, convulsions, and cardiac stimulation or depression should be immediately available [see Warnings and Precautions (5.14)]. As with other anesthetic procedures, patients should be constantly monitored following ophthalmic blocks for signs of these adverse reactions, which may occur following relatively low total doses.

A concentration of 0.75% bupivacaine is indicated for retrobulbar block; however, this concentration is not indicated for any other peripheral nerve block, including the facial nerve, and not indicated for local infiltration, including the conjunctiva [see Indications and Usage (1)].

5.16 Risk of Inadvertent Trauma to Tongue, Lips, and Buccal Mucosa in Dental Applications

Because of the long duration of anesthesia, when MARCAINE WITH EPINEPHRINE [0.5% (5 mg/mL) of bupivacaine] is used for dental injections, warn patients about the possibility of inadvertent trauma to tongue, lips, and buccal mucosa and advise them not to chew solid foods until sensation returns [see PATIENT COUNSELING INFORMATION (17)].

6 Adverse Reactions

The following clinically significant adverse reactions have been reported and described in the Warnings and Precautions section of the labeling:

- Cardiac Arrest in Obstetrical Anesthesia [see Warnings and Precautions (5.1)]
- Dose-Related Toxicity [see Warnings and Precautions (5.2)]
- Methemoglobinemia [see Warnings and Precautions (5.3)]
- Chondrolysis with Intra-Articular Infusion [see Warnings and Precautions (5.5)]
- Severe, Persistent Hypertension, Cerebrovascular Accidents, and Bradycardia Due to Drug Interactions [see Warnings and Precautions (5.6)]
- Cardiac Arrest with Intravenous Regional Anesthesia Use [see Contraindications (4), Warnings and Precautions (5.7)]
- Allergic-Type Reactions [see WARNINGS AND PRECAUTIONS (5.8)]
- Systemic Toxicities with Unintended Intravascular or Intrathecal Injection [see Warnings and Precautions (5.9)]
- Respiratory Arrest Following Retrobulbar Block [see Warnings and Precautions (5.15)]

The following adverse reactions from voluntary reports or clinical studies have been reported with bupivacaine or bupivacaine and epinephrine. Because many of these reactions were reported voluntarily from a population of uncertain size, it is not always possible to reliably estimate their frequency or establish a causal relationship to drug exposure.

Adverse reactions to MARCAINE / MARCAINE WITH EPINEPRHINE are characteristic of those associated with other amide-type local anesthetics. A major cause of adverse reactions to this group of drugs is excessive plasma levels, which may be due to overdosage, unintentional intravascular injection, or slow metabolic degradation.

The most commonly encountered acute adverse reactions that demand immediate counter-measures were related to the CNS and the cardiovascular system. These adverse reactions were generally dose-related and due to high plasma levels which may have resulted from overdosage, rapid absorption from the injection site, diminished tolerance, or from unintentional intravascular injection of the local anesthetic solution. In addition to systemic dose-related toxicity, unintentional intrathecal injection of drug during the intended performance of caudal or lumbar epidural block or nerve blocks near the vertebral column (especially in the head and neck region) has resulted in underventilation or apnea ("Total or High Spinal"). Also, hypotension due to loss of sympathetic tone and respiratory paralysis or underventilation due to cephalad extension of the motor level of anesthesia have occurred. This has led to secondary cardiac arrest when untreated.

Nervous System Disorders: Adverse reactions were characterized by excitation and/or depression of the central nervous system and included restlessness, anxiety, dizziness, tinnitus, blurred vision, tremors, convulsions, drowsiness, unconsciousness, respiratory arrest, nausea, vomiting, chills, pupillary constriction.

In the practice of caudal or lumbar epidural block, unintentional penetration of the subarachnoid space by the catheter or needle has occurred. Subsequent adverse effects may have depended partially on the amount of drug administered intrathecally and the physiological and physical effects of a dural puncture. A high spinal has been characterized by paralysis of the legs, loss of consciousness, respiratory paralysis, and bradycardia.

Neurologic effects following epidural or caudal anesthesia have included spinal block of varying magnitude (including high or total spinal block); hypotension secondary to spinal block; urinary retention; fecal and urinary incontinence; loss of perineal sensation and sexual function; persistent anesthesia, paresthesia, weakness, paralysis of the lower extremities and loss of sphincter control, all of which had slow, incomplete, or no recovery; headache; backache; septic meningitis; meningismus; slowing of labor; increased incidence of forceps delivery; and cranial nerve palsies due to traction on nerves from loss of cerebrospinal fluid.

Neurologic effects following other procedures or routes of administration have included persistent anesthesia, paresthesia, weakness, paralysis, all with slow, incomplete, or no recovery.

Convulsions: Incidence varied with the procedure used and the total dose administered. In a survey of studies of epidural anesthesia, overt toxicity progressing to convulsions occurred in approximately 0.1% of local anesthetic administrations. The incidences of adverse neurologic reactions associated with the use of local anesthetics may be related to the total dose of local anesthetic administered and are also dependent upon the particular drug used, the route of administration, and the physical status of the patient.

Cardiac Disorders: High doses or unintentional intravascular injection have led to high plasma levels and related depression of the myocardium, decreased cardiac output, heartblock, hypotension, bradycardia, ventricular arrhythmias, including ventricular tachycardia and ventricular fibrillation, and cardiac arrest [see Warnings and Precautions (5.9)].

Immune System Disorders: Allergic-type reactions have occurred as a result of sensitivity to bupivacaine or to other formulation ingredients, such as the antimicrobial preservative methylparaben contained in multiple-dose vials or sulfites in epinephrine-containing solutions. These reactions were characterized by signs such as urticaria, pruritus, erythema, angioneurotic edema (including laryngeal edema), tachycardia, sneezing, nausea, vomiting, dizziness, syncope, excessive sweating, elevated temperature, and severe hypotension. Cross sensitivity among members of the amide-type local anesthetic group has been reported [see Warnings and Precautions (5.8)].

7 Drug Interactions

7.1 Local Anesthetics

The toxic effects of local anesthetics are additive. If coadministration of other local anesthetics with MARCAINE / MARCAINE WITH EPINEPHRINE cannot be avoided, monitor patients for neurologic and cardiovascular effects related to local anesthetic systemic toxicity [see Dosage and Administration (2.1), Warnings and Precautions (5.2)].

7.2 Monoamine Oxidase Inhibitors and Tricyclic Antidepressants

The administration of MARCAINE WITH EPINEPHRINE to patients receiving monoamine oxidase inhibitors, or tricyclic antidepressants may produce severe, prolonged hypertension. Concurrent use of these agents should generally be avoided. In situations when concurrent therapy is necessary, careful monitoring of the patient's hemodynamic status is essential [see Warnings and Precautions (5.6)].

7.3 Ergot-Type Oxytocic Drugs

Concurrent administration of MARCAINE WITH EPINEPHRINE and ergot-type oxytocic drugs may cause severe, persistent hypertension or cerebrovascular accidents. Avoid use of MARCAINE WITH EPINEPHRINE concomitantly with ergot-type oxytocic drugs [see Warnings and Precautions (5.6)].

7.4 Nonselective Beta-Adrenergic Antagonists

Administration of MARCAINE WITH EPINEPHRINE (containing a vasoconstrictor) in patients receiving nonselective beta-adrenergic antagonists Administration of MARCAINE WITH EPINEPHRINE (containing a vasoconstrictor) in patients receiving nonselective beta-adrenergic antagonists may cause severe hypertension and bradycardia. Concurrent use of these agents should generally be avoided. In situations when concurrent therapy is necessary, careful monitoring of the patient's blood pressure and heart rate is essential [see Warnings and Precautions (5.6)].

7.5 Drugs Associated with Methemoglobinemia

Patients who are administered MARCAINE / MARCAINE WITH EPINEPHRINE are at increased risk of developing methemoglobinemia when concurrently exposed to following drugs, which could include other local anesthetics [see Warnings and Precautions (5.3)].

7.6 Potent Inhalation Anesthetics

Serious dose-related cardiac arrhythmias may occur if preparations containing a vasoconstrictor such as epinephrine (e.g., MARCAINE WITH EPINEPHRINE) are used in patients during or following the administration of potent inhalation anesthetics [see Warnings and Precautions (5.13)].

7.7 Phenothiazines and Butyrophenones

Phenothiazines and butyrophenones may reduce or reverse the pressor effect of epinephrine. Concurrent use of MARCAINE WITH EPINEPHRINE and these agents should generally be avoided. In situations when concurrent therapy is necessary, careful patient monitoring is essential.

8 USE IN SPECIFIC POPULATIONS

8.1 Pregnancy

Risk Summary

MARCAINE / MARCAINE WITH EPINEPHRINE is contraindicated for obstetrical paracervical block anesthesia. Its use in this technique has resulted in fetal bradycardia and death [see Contraindications (4), Warnings and Precautions (5.1)].

There are no available data on use of MARCAINE / MARCAINE WITH EPINEPHRINE in pregnant women to inform a drug-associated risk of adverse developmental outcomes.

In animal studies, embryo-fetal lethality was noted when bupivacaine was administered subcutaneously to pregnant rabbits during organogenesis at clinically relevant doses. Decreased pup survival was observed in a rat pre- and post-natal developmental study (dosing from implantation through weaning) at a dose level comparable to the daily maximum recommended human dose (MRHD) on a body surface area (BSA) basis. Based on animal data, advise pregnant women of the potential risks to a fetus (see Data).

Local anesthetics rapidly cross the placenta, and when used for epidural, caudal, or pudendal block anesthesia, can cause varying degrees of maternal, fetal, and neonatal toxicity [see Clinical Pharmacology (12.3)]. The incidence and degree of toxicity depend upon the procedure performed, the type, and amount of drug used, and the technique of drug administration. Adverse reactions in the parturient, fetus, and neonate involve alterations of the CNS, peripheral vascular tone, and cardiac function.

If this drug is used during pregnancy, or if the patient becomes pregnant while taking this drug, inform the patient of the potential hazard to the fetus. The estimated background risk of major birth defects and miscarriage for the indicated populations are unknown. In the U.S. general population, the estimated background risk of major birth defects and miscarriage in clinically recognized pregnancies is 2–4% and 15–20%, respectively.

Clinical Considerations

Maternal Adverse Reactions

Maternal hypotension has resulted from regional anesthesia. Local anesthetics produce vasodilation by blocking sympathetic nerves. The supine position is dangerous in pregnant women at term because of aortocaval compression by the gravid uterus. Therefore, during treatment of systemic toxicity, maternal hypotension or fetal bradycardia following regional block, the parturient should be maintained in the left lateral decubitus position if possible, or manual displacement of the uterus off the great vessels be accomplished. Elevating the patient's legs will also help prevent decreases in blood pressure. The fetal heart rate also should be monitored continuously and electronic fetal monitoring is highly advisable.

Labor or Delivery

Epidural, caudal, or pudendal anesthesia may alter the forces of parturition through changes in uterine contractility or maternal expulsive efforts. Epidural anesthesia has been reported to prolong the second stage of labor by removing the parturient's reflex urge to bear down or by interfering with motor function. The use of obstetrical anesthesia may increase the need for forceps assistance.

The use of some local anesthetic drug products during labor and delivery may be followed by diminished muscle strength and tone for the first day or two of life. This has not been reported with bupivacaine.

It is extremely important to avoid aortocaval compression by the gravid uterus during administration of regional block to parturients. To do this, the patient must be maintained in the left lateral decubitus position or a blanket roll or sandbag may be placed beneath the right hip and gravid uterus displaced to the left.

Data

Animal Data

Bupivacaine hydrochloride produced developmental toxicity when administered subcutaneously to pregnant rats and rabbits at clinically relevant doses.

Bupivacaine hydrochloride was administered subcutaneously to rats at doses of 4.4, 13.3, & 40 mg/kg and to rabbits at doses of 1.3, 5.8, & 22.2 mg/kg during the period of organogenesis (implantation to closure of the hard palate). The high doses are comparable to the daily MRHD of 400 mg/day on a mg/m^2 BSA basis. No embryo-fetal effects were observed in rats at the high dose which caused increased maternal lethality. An increase in embryo-fetal deaths was observed in rabbits at the high dose in the absence of maternal toxicity with the fetal No Observed Adverse Effect Level representing approximately 0.3 times the MRHD on a BSA basis.

In a rat pre- and post-natal developmental study (dosing from implantation through weaning) conducted at subcutaneous doses of 4.4, 13.3, & 40 mg/kg, decreased pup survival was observed at the high dose. The high dose is comparable to the daily MRHD of 400 mg/day on a BSA basis.

8.2 Lactation

Risk Summary

Lactation studies have not been conducted with bupivacaine. Bupivacaine has been reported to be excreted in human milk suggesting that the nursing infant could be theoretically exposed to a dose of the drug. MARCAINE / MARCAINE WITH EPINEPHRINE should be administered to lactating women only if clearly indicated. Studies assessing the effects of MARCAINE / MARCAINE WITH EPINEPHRINE in breastfed children have not been performed. Studies to assess the effect of MARCAINE / MARCAINE WITH EPINEPHRINE on milk production or excretion have not been performed. The developmental and health benefits of breastfeeding should be considered along with the mother's clinical need for bupivacaine and any potential adverse effects on the breastfed child from bupivacaine or from the underlying maternal condition.

8.4 Pediatric Use

MARCAINE / MARCAINE WITH EPINEPHRINE is approved for use in adults. Administration of MARCAINE / MARCAINE WITH EPINEPHRINE in pediatric patients younger than 12 years is not recommended.

Continuous infusions of bupivacaine in pediatric patients have been reported to result in high systemic levels of bupivacaine and seizures; high plasma levels may also be associated with cardiovascular abnormalities.

8.5 Geriatric Use

Patients 65 years and over, particularly those with hypertension, may be at increased risk for developing hypotension while undergoing anesthesia with MARCAINE / MARCAINE WITH EPINEPHRINE.

In clinical studies of bupivacaine, elderly patients reached the maximal spread of analgesia and maximal motor blockade more rapidly than younger adult patients.

Differences in various pharmacokinetic parameters have been observed between elderly and younger adult patients [see Clinical Pharmacology (12.3)].

This product is known to be substantially excreted by the kidney, and the risk of adverse reactions to this drug may be greater in patients with impaired renal function. Because elderly patients are more likely to have decreased renal function, care should be taken in dose selection, and it may be useful to monitor renal function. Elderly patients may require lower doses of MARCAINE / MARCAINE WITH EPINEPHRINE.

8.6 Hepatic Impairment

Amide-type local anesthetics, such as bupivacaine, are metabolized by the liver. Patients with severe hepatic impairment, because of their inability to metabolize local anesthetics normally, are at a greater risk of developing toxic plasma concentrations, and potentially local anesthetic systemic toxicity. Therefore, consider reduced dosing and increased monitoring for local anesthetic systemic toxicity in patients with moderate to severe hepatic impairment treated with MARCAINE / MARCAINE WITH EPINEPHRINE, especially with repeat doses [see Warnings and Precautions (5.10)].

8.7 Renal Impairment

Bupivacaine is known to be substantially excreted by the kidney, and the risk of adverse reactions to this drug may be greater in patients with renal impairment. This should be considered when selecting the MARCAINE / MARCAINE WITH EPINEPHRINE dosage [see Use in Specific Populations (8.5)].

10 Overdosage

Clinical Presentation

Acute emergencies from use of MARCAINE / MARCAINE WITH EPINEPHRINE are generally related to high plasma levels encountered during therapeutic use or to unintended intrathecal injection [see Warnings and Precautions (5.2, 5.9), Adverse Reactions (6)].

If not treated immediately, convulsions with simultaneous hypoxia, hypercarbia, and acidosis plus myocardial depression from the direct effects of bupivacaine may result in cardiac arrhythmias, bradycardia, asystole, ventricular fibrillation, or cardiac arrest. Respiratory abnormalities, including apnea, may occur. Hypoventilation or apnea due to unintentional intrathecal injection of MARCAINE / MARCAINE WITH EPINEPHRINE may produce these same signs and also lead to cardiac arrest if ventilatory support is not instituted. If cardiac arrest should occur, successful outcome may require prolonged resuscitative efforts.

Management

The first step in the management of systemic toxic reactions, as well as hypoventilation or apnea due to unintentional intrathecal injection of MARCAINE / MARCAINE WITH EPINEPHRINE, consists of immediate attention to the establishment and maintenance of a patent airway and effective assisted or controlled ventilation with 100% oxygen with a delivery system capable of permitting immediate positive airway pressure by mask. Endotracheal intubation, using drugs and techniques familiar to the clinician, may be indicated after initial administration of oxygen by mask if difficulty is encountered in the maintenance of a patent airway, or if prolonged ventilatory support (assisted or controlled) is indicated.

If necessary, use drugs to manage the convulsions. A bolus intravenous dose of a benzodiazepine will counteract CNS stimulation related to MARCAINE. Immediately after the institution of ventilatory measures, evaluate the adequacy of the circulation. Supportive treatment of circulatory depression may require Advanced Cardiac Life Support measures.

11 Description

MARCAINE / MARCAINE WITH EPINEPHRINE contains bupivacaine hydrochloride, an amide local anesthetic, as the active pharmaceutical ingredient. The route of administration for MARCAINE (without epinephrine) is by injection, for infiltration, perineural, caudal, epidural, or retrobulbar use. The route of administration for MARCAINE WITH EPINEPHRINE is by injection, for infiltration, perineural, caudal, or epidural use. Multiple-dose vials contain methylparaben [see Warnings and Precautions (5.4)].

Bupivacaine hydrochloride is 2-piperidinecarboxamide, 1-butyl-N-(2,6-dimethylphenyl)-, monohydrochloride, monohydrate. It is a white crystalline powder that is freely soluble in 95 percent ethanol, soluble in water, and slightly soluble in chloroform or acetone. It has the following structural formula:

MARCAINE with 1:200,000 epinephrine, contains bupivacaine hydrochloride and epinephrine bitartrate (an alpha and beta-adrenergic agonist) as active pharmaceutical ingredients. This product is for injection via local infiltration, peripheral nerve block, and caudal and lumbar epidural blocks. Multiple dose vials contain methylparaben and they should not be used for caudal and lumbar epidural blocks.

Epinephrine bitartrate is (–) - 3,4-Dihydroxy-α-[(methylamino)methyl] benzyl alcohol (+)-tartrate (1:1) salt. Epinephrine is a vasoconstrictor. It has the following structural formula:

MARCAINE (bupivacaine hydrochloride) is a clear and colorless sterile isotonic solution. Each mL of single-dose vial contains 2.5 mg, 5 mg or 7.5 mg of bupivacaine hydrochloride (equivalent to 2.22 mg, 4.44 mg or 6.66 mg of bupivacaine, respectively), sodium chloride for isotonicity, sodium hydroxide or hydrochloric acid to adjust the pH between 4 and 6.5, in water for injection.

For the Multiple-dose vials, each mL also contains 1 mg methylparaben as preservative.

MARCAINE with epinephrine 1:200,000 (as bitartrate) is a clear and colorless sterile isotonic solution. Each mL contains 2.5 mg or 5 mg bupivacaine hydrochloride (equivalent to 2.22 mg or 4.44 mg of bupivacaine, respectively), and 0.0091 mg epinephrine bitartrate (equivalent to 0.005 mg of epinephrine), with sodium chloride for isotonicity, 0.5 mg sodium metabisulfite, 0.001 mL monothioglycerol, and 2 mg ascorbic acid as antioxidants, 0.0017 mL 60% sodium lactate buffer, and 0.1 mg edetate calcium disodium as stabilizer. The pH of these solutions is adjusted to between 3.4 and 4.5 with sodium hydroxide or hydrochloric acid.

For the Multiple-dose vials, each mL also contains 1 mg methylparaben as preservative.

The specific gravity of MARCAINE 0.5% with epinephrine 1:200,000 (as bitartrate) at 25°C is 1.008 and at 37°C is 1.008.

12 Clinical Pharmacology

12.1 Mechanism of Action

Bupivacaine blocks the generation and the conduction of nerve impulses, presumably by increasing the threshold for electrical excitation in the nerve, by slowing the propagation of the nerve impulse, and by reducing the rate of rise of the action potential. In general, the progression of anesthesia is related to the diameter, myelination, and conduction velocity of affected nerve fibers. Clinically, the order of loss of nerve function is as follows: (1) pain, (2) temperature, (3) touch, (4) proprioception, and (5) skeletal muscle tone.

Epinephrine is a vasoconstrictor added to bupivacaine to slow absorption into the general circulation and thus prolong maintenance of an active tissue concentration.

12.2 Pharmacodynamics

Systemic absorption of bupivacaine produces effects on the cardiovascular system and CNS. At blood concentrations achieved with normal therapeutic doses, changes in cardiac conduction, excitability, refractoriness, contractility, and peripheral vascular resistance are minimal. However, toxic blood concentrations depress cardiac conduction and excitability, which may lead to atrioventricular block, ventricular arrhythmias, and cardiac arrest, sometimes resulting in fatalities. In addition, myocardial contractility is depressed and peripheral vasodilation occurs, leading to decreased cardiac output and arterial blood pressure. These cardiovascular changes are more likely to occur after unintended intravascular injection of bupivacaine [see Warnings and Precautions (5.9)].

Following systemic absorption, bupivacaine can produce CNS stimulation, CNS depression, or both. Apparent central stimulation is manifested as restlessness, tremors, and shivering, progressing to convulsions, followed by CNS depression and coma progressing ultimately to respiratory arrest. However, bupivacaine has a primary depressant effect on the medulla and on higher centers. The depressed stage may occur without a prior excited state.

The duration of local anesthesia after administration of MARCAINE is longer than that observed after administration of other commonly used short-acting local anesthetics. There appears to be period of analgesia that persists after the resolution of the block and return of sensation.

The onset of action following dental injections is usually 2 to 10 minutes and may last up to 7 hours. The duration of anesthetic effect is prolonged by the addition of epinephrine 1:200,000.

12.3 Pharmacokinetics

Systemic plasma levels of bupivacaine following administration of MARCAINE do not correlate with local efficacy.

Absorption

The rate of systemic absorption of bupivacaine is dependent upon the total dose and concentration of drug administered, the route of administration, the vascularity of the administration site, and the presence or absence of epinephrine in the anesthetic solution. A dilute concentration of epinephrine (1:200,000) usually reduces the rate of absorption and peak plasma concentration of bupivacaine, permitting the use of moderately larger total doses and sometimes prolonging the duration of action [see Dosage and Administration (2)].

After injection of MARCAINE for caudal, epidural, or peripheral nerve block, peak levels of bupivacaine in the blood are reached in 30 to 45 minutes, followed by a decline to insignificant levels during the next three to six hours.

Distribution

Bupivacaine appears to cross the placenta by passive diffusion. The rate and degree of diffusion is governed by (1) the degree of plasma protein binding, (2) the degree of ionization, and (3) the degree of lipid solubility. Fetal/ maternal ratios of bupivacaine appear to be inversely related to the degree of plasma protein binding, because only the free, unbound drug is available for placental transfer. Bupivacaine with a high protein binding capacity (95%) has a low fetal/maternal ratio (0.2 to 0.4). The extent of placental transfer is also determined by the degree of ionization and lipid solubility of the drug. Lipid soluble, nonionized drugs readily enter the fetal blood from the maternal circulation.

Depending upon the route of administration, bupivacaine is distributed to some extent to all body tissues, with high concentrations found in highly perfused organs such as the liver, lungs, heart, and brain.

Pharmacokinetic studies on the plasma profile of bupivacaine after direct intravenous injection (MARCAINE is not approved for intravenous use) suggest a three-compartment open model. The first compartment is represented by the rapid intravascular distribution of the drug. The second compartment represents the equilibration of the drug throughout the highly perfused organs such as the brain, myocardium, lungs, kidneys, and liver. The third compartment represents an equilibration of the drug with poorly perfused tissues, such as muscle and fat.

Elimination

The half-life of bupivacaine in adults is 2.7 hours.

Metabolism

Amide-type local anesthetics such as bupivacaine are metabolized primarily in the liver via conjugation with glucuronic acid. Pipecoloxylidine is the major metabolite of bupivacaine. The elimination of drug from tissue distribution depends largely upon the availability of binding sites in the circulation to carry it to the liver where it is metabolized.

Excretion

The kidney is the main excretory organ for most local anesthetics and their metabolites. Urinary excretion is affected by urinary perfusion and factors affecting urinary pH. Only 6% of bupivacaine is excreted unchanged in the urine.

Specific Populations

Geriatric Patients

Elderly patients exhibited higher peak plasma concentrations than younger patients following administration of MARCAINE. The total plasma clearance was decreased in these patients [see Use In Specific Populations (8.5)].

Patients with Hepatic Impairment

Various pharmacokinetic parameters of the local anesthetics can be significantly altered by the presence of hepatic disease. Patients with hepatic disease, especially those with severe hepatic disease, may be more susceptible to the potential toxicities of the amide-type local anesthetics [see Use In Specific Populations (8.6)].

Patients with Renal Impairment

Various pharmacokinetic parameters of the local anesthetics can be significantly altered by the presence of renal disease, factors affecting urinary pH, and renal blood flow [see Use In Specific Populations(8.5, 8.7)].

13 Nonclinical Toxicology

13.1 Carcinogenesis, Mutagenesis, Impairment of Fertility

Carcinogenesis

Long-term studies in animals to evaluate the carcinogenic potential of bupivacaine hydrochloride have not been conducted.

Mutagenesis

The mutagenic potential of bupivacaine hydrochloride has not been determined.

Impairment of Fertility

The effect of bupivacaine on fertility has not been determined.

16 How Supplied/Storage and Handling

Store at 20°C to 25°C (68°F to 77°F); excursions permitted between 15°C to 30°C (59°F to 86°F). [See USP Controlled Room Temperature.]

MARCAINE—Solutions of MARCAINE that do not contain epinephrine may be autoclaved. Autoclave at 15-pound pressure, 121°C (250°F) for 15 minutes. This product is clear and colorless. Do not use the solution if it is discolored or if it contains a precipitate.

For single-dose vials: Discard unused portion.

MARCAINE with epinephrine 1:200,000 (as bitartrate)—Do not autoclave solutions of MARCAINE that contain epinephrine and protect from light. This product is clear and colorless. Do not use the solution if it is discolored or if it contains a precipitate.

For single-dose vials: Discard unused portion.

Product repackaged by: Henry Schein, Inc., Bastian, VA 24314
From Original Manufacturer/Distributor's NDC and Unit of Sale | To Henry Schein Repackaged Product NDC and Unit of Sale | Total Strength/Total Volume (Concentration) per unit
NDC 0409-1746-30 Carton of 10 | NDC 0404-9908-30 1 single-dose vial in a bag (Vial bears NDC 0409-1746-71) | 0.25% with epinephrine 1:200,000-Contains 2.5 mg bupivacaine hydrochloride per mL 75 mg/30 mL (2.5 mg/mL)

Patient Counseing Information

Allergic-Type Reactions

Assess if the patient has had allergic-type reactions to amide-type local anesthetics or to other formulation ingredients, such as the antimicrobial preservative methylparaben contained in multiple-dose vials or sulfites in epinephrine-containing solutions [see Contraindications (4), Warnings and Precautions (5.8), Adverse Reactions (6)].

Temporary Loss of Sensation and Motor Activity After Caudal or Epidural Anesthesia

When appropriate, patients should be informed in advance that they may experience temporary loss of sensation and motor activity, usually in the lower half of the body, following proper administration of caudal or epidural anesthesia.

Instructions After Dental Injection of MARCAINE

Advise patients receiving dental injections of MARCAINE not to chew solid foods or to test the anesthetized area by biting or probing until anesthesia has worn off (up to 7 hours) [see Warnings and Precautions (5.16)].

Methemoglobinemia

Inform patients that use of local anesthetics may cause methemoglobinemia, a serious condition that must be treated promptly. Advise patients or caregivers to seek immediate medical attention if they or someone in their care experience the following signs or symptoms: pale, gray, or blue colored skin (cyanosis); headache; rapid heart rate; shortness of breath; lightheadedness; or fatigue [see Warnings and Precautions (5.3)].

This product's labeling may have been updated. For the most recent prescribing information, please visit www.pfizer.com.

For medical information about MARCAINE / MARCAINE WITH EPINEPHRINE, please visit www.pfizermedinfo.com or call 1-800-438-1985.

Distributed by Hospira, Inc., Lake Forest, IL 60045 USA

LAB-1178-6.0